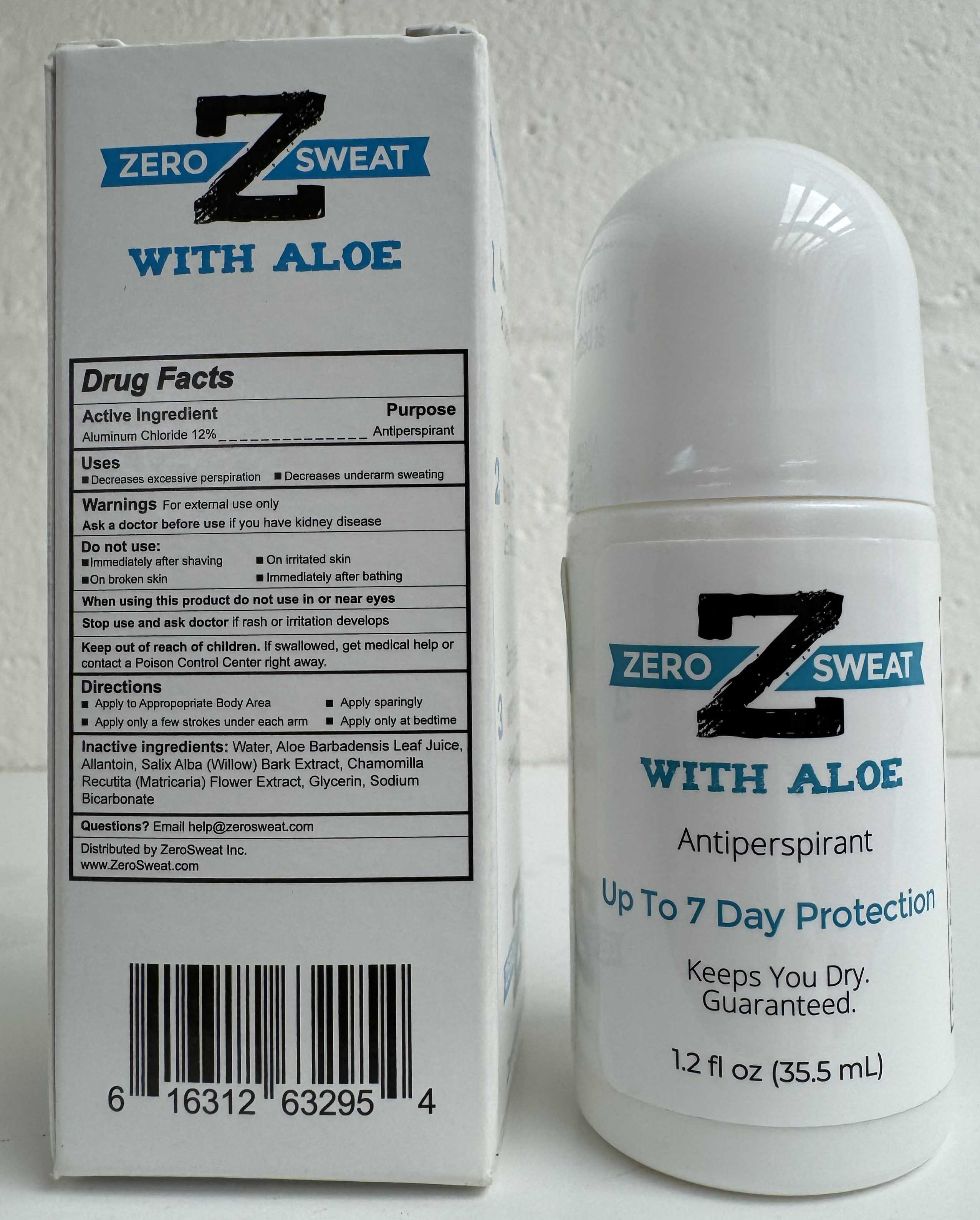 DRUG LABEL: ZeroSweat Antiperspirant 12%
NDC: 65112-306 | Form: LOTION
Manufacturer: I. Shay Cosmetics
Category: otc | Type: HUMAN OTC DRUG LABEL
Date: 20241113

ACTIVE INGREDIENTS: ALUMINUM CHLORIDE 0.12 g/35.5 mL
INACTIVE INGREDIENTS: WATER

Zerosweat Antiperspirant 12% 1.2oz

ACTIVE INGREDIENT

Aluminum Chloride- 12%

PURPOSE

Antiperspirant

WARNING: Keep out of reach of children

INDICATIONS AND USAGE

Decreases excessive perspiration.

Decreases underarm sweating.

INACTIVE INGREDIENT

Purified Water, Aloe Vera Extract, Allantoin, Willow Bark Extract, Chamomile Extract, Glycerin, Sodium Bicarbonate.

WARNINGS

For External Use Only.

Ask a doctor before use if you have kidney disease.

Do not use:

-Immediately after shaving

-On irritated skin

-On broken skin

-Immediately after bathing

When using this product do not use in or near eyes.

Stop use and ask doctor if rash or irritation develops

Keep out of reach of children.

If swallowed, get medical help or contact a Poison Control Center right away.

DOSAGE AND ADMINISTRATION

Apply to appropriate body area. Apply sparingly. Apply only a few strokes under each arm. Apply only at bedtime.